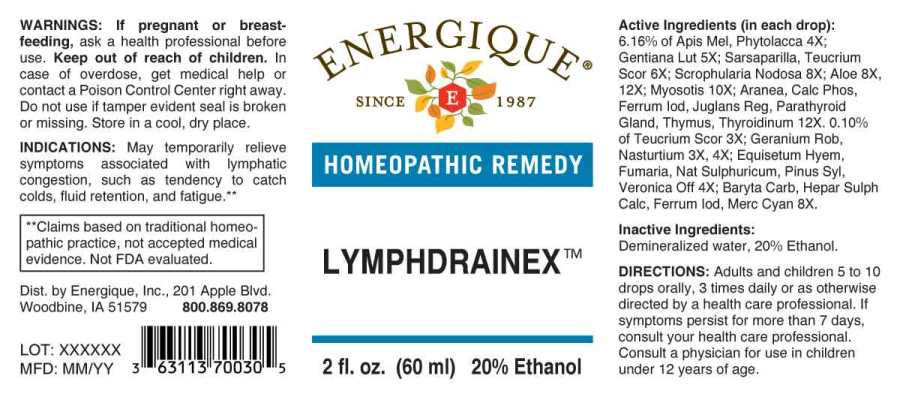 DRUG LABEL: LYMPHDRAINEX
NDC: 44911-0638 | Form: LIQUID
Manufacturer: Energique, Inc.
Category: homeopathic | Type: HUMAN OTC DRUG LABEL
Date: 20231212

ACTIVE INGREDIENTS: GERANIUM ROBERTIANUM WHOLE 3 [hp_X]/1 mL; NASTURTIUM OFFICINALE 3 [hp_X]/1 mL; TEUCRIUM SCORODONIA FLOWERING TOP 3 [hp_X]/1 mL; APIS MELLIFERA 4 [hp_X]/1 mL; EQUISETUM HYEMALE WHOLE 4 [hp_X]/1 mL; FUMARIA OFFICINALIS FLOWERING TOP 4 [hp_X]/1 mL; SODIUM SULFATE 4 [hp_X]/1 mL; PHYTOLACCA AMERICANA ROOT 4 [hp_X]/1 mL; PINUS SYLVESTRIS LEAFY TWIG 4 [hp_X]/1 mL; VERONICA OFFICINALIS FLOWERING TOP 4 [hp_X]/1 mL; GENTIANA LUTEA ROOT 5 [hp_X]/1 mL; SMILAX ORNATA ROOT 6 [hp_X]/1 mL; BARIUM CARBONATE 8 [hp_X]/1 mL; CALCIUM SULFIDE 8 [hp_X]/1 mL; MERCURIC CYANIDE 8 [hp_X]/1 mL; SCROPHULARIA NODOSA WHOLE 8 [hp_X]/1 mL; ALOE 8 [hp_X]/1 mL; FERROUS IODIDE 8 [hp_X]/1 mL; MYOSOTIS ARVENSIS WHOLE 10 [hp_X]/1 mL; ARANEUS DIADEMATUS 12 [hp_X]/1 mL; TRIBASIC CALCIUM PHOSPHATE 12 [hp_X]/1 mL; JUGLANS REGIA LEAF 12 [hp_X]/1 mL; BOS TAURUS PARATHYROID GLAND 12 [hp_X]/1 mL; SUS SCROFA THYMUS 12 [hp_X]/1 mL; SUS SCROFA THYROID 12 [hp_X]/1 mL
INACTIVE INGREDIENTS: WATER; ALCOHOL

DRUG FACTS:

ACTIVE INGREDIENTS:

(in each drop): 6.16% of Apis Mellifica 4X, Phytolacca Decandra 4X; Gentiana Lutea 5X; Sarsaparilla (Smilax Regelii) 6X, Teucrium Scorodonia 6X; Scrophularia Nodosa 8X; Aloe 8X, 12X; Myosotis Arvensis 10X; Aranea Diadema 12X, Calcarea Phosphorica 12X, Ferrum Iodatum 12X, Juglans Regia 12X, Parathyroid Gland (Bovine)12X, Thymus (Suis) 12X, Thyroidinum (Suis) 12X. 0.10% of Teucrium Scorodonia 3X; Geranium Robertianum 3X, 4X; Equisetum Hyemale 4X, Fumaria Officinalis 4X, Natrum Sulphuricum 4X, Pinus Sylvestris 4X, Veronica Officinalis 4X; Baryta Carbonica 8X, Hepar Sulphuris Calcareum 8X, Ferrum Iodatum 8X, Mercurius Cyanatus 8X.

INDICATIONS:

May temporarily relieve symptoms associated with lymphatic congestion, such as tendency to catch colds, fluid retention, and fatigue.**

**Claims based on traditional homeopathic practice, not accepted medical evidence. Not FDA evaluated.

WARNINGS:

If pregnant or breast-feeding, ask a health professional before use.

Keep out of reach of children. In case of overdose, get medical help or contact a Poison Control Center right away.

Do not use if tamper evident seal is broken or missing.

Store in a cool, dry place.

Keep out of reach of children. In case of overdose, get medical help or contact a Poison Control Center right away.

DIRECTIONS:

Adults and children 5 to 10 drops orally, 3 times daily or as otherwise directed by a health care professional. If symptoms persist for more than 7 days, consult your health care professional. Consult a physician for use in children under 12 years of age.

INDICATIONS:

May temporarily relieve symptoms associated with lymphatic congestion, such as tendency to catch colds, fluid retention, and fatigue.**

**Claims based on traditional homeopathic practice, not accepted medical evidence. Not FDA evaluated.

INACTIVE INGREDIENTS:

Demineralized water, 20% Ethanol.

QUESTIONS:

Dist. by Energique, Inc.

201 Apple Blvd.

Woodbine, IA 51579 800.869.8078

PACKAGE LABEL DISPLAY:

ENERGIQUE

SINCE 1987

HOMEOPATHIC REMEDY

LYMPHDRAINEX

2 fl. oz. (60 ml)